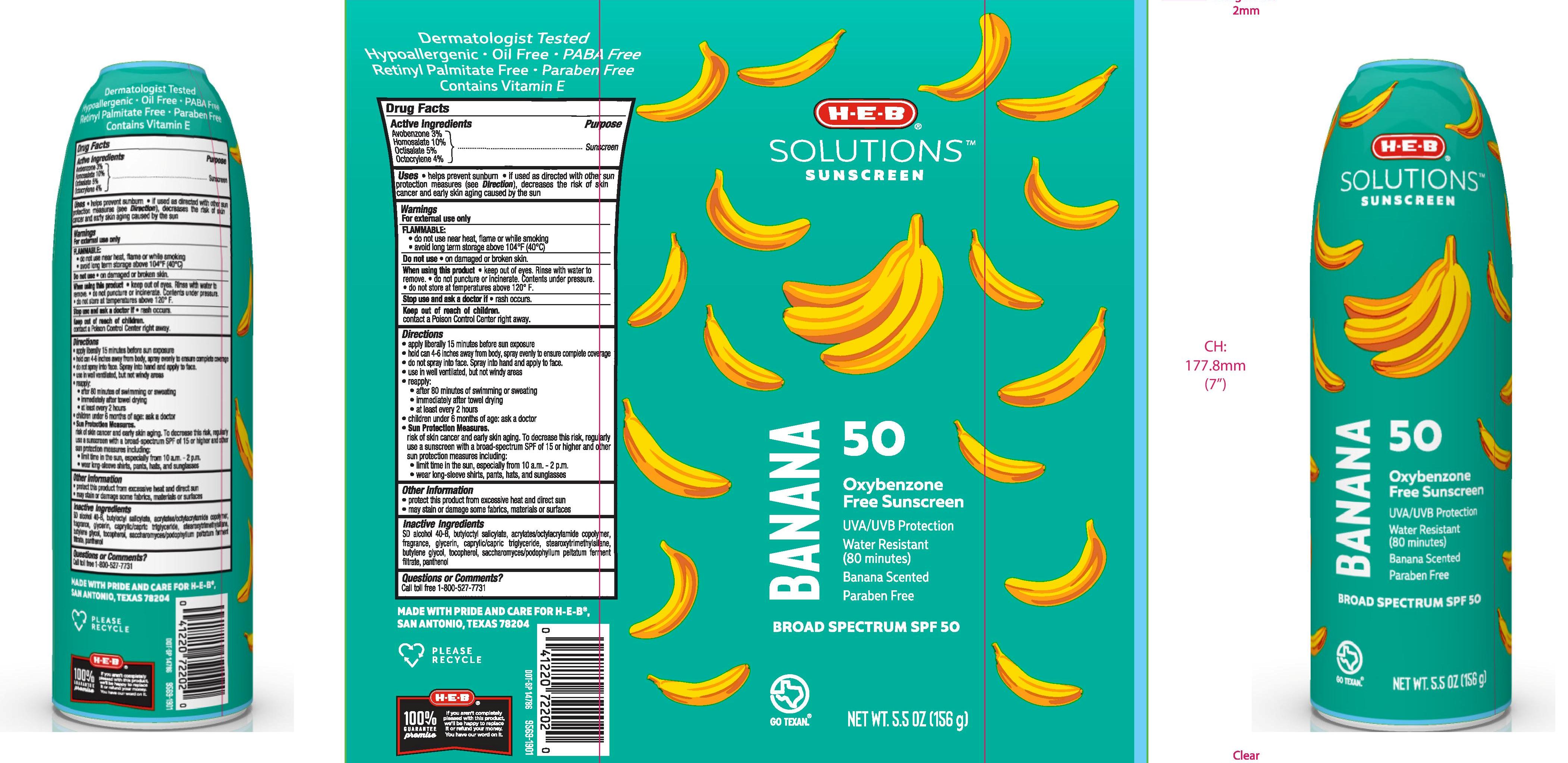 DRUG LABEL: H.E.B
NDC: 37808-912 | Form: AEROSOL, SPRAY
Manufacturer: H.E.B
Category: otc | Type: HUMAN OTC DRUG LABEL
Date: 20241015

ACTIVE INGREDIENTS: AVOBENZONE 30 mg/1 g; HOMOSALATE 100 mg/1 g; OCTISALATE 50 mg/1 g; OCTOCRYLENE 40 mg/1 g
INACTIVE INGREDIENTS: ALCOHOL; ACRYLATE/ISOBUTYL METHACRYLATE/N-TERT-OCTYLACRYLAMIDE COPOLYMER (75000 MW); TOCOPHEROL; GLYCERIN; STEAROXYTRIMETHYLSILANE; MEDIUM-CHAIN TRIGLYCERIDES; BUTYLENE GLYCOL; BUTYLOCTYL SALICYLATE; PANTHENOL

H-E-B SOLUTIONS SUNSCREEN BANANA SPF 50 CONTINUOUS SPRAY

Active Ingredients

Avobenzone 3.0%, Homosalate 10.0%, Octisalate 5.0%, Octocrylene 4.0%

Purpose

Sunscreen

Uses

- helps prevent sunburn
- if used as directed with other sun protetion measures (see Directions), decreases the risk of skin cancer and early skin aging caused by the sun

Warnings

For external use only

FLAMMABLE:

- do not use near heat, flame or while smoking
- avoid long term stoage above 104°F (40°C)

Do not use • on damaged or broken skin.

When using this product • keep out of eyes. Rinse with water to remove. • do not puncture or incinerate. Contents under pressure. • do not store at temperatures above 120°F.

Stop use and ask a doctor if • rash occurs.

Keep out of reach of children. if swallowed, get medical help or contact a Poison Control Center right away.

Directions

- apply liberally 15 minutes before sun exposure
- hold can 4-6 inches away from body, spray evenly to ensure complete coverage
- do not spray into face. Spray into hand and apply to face.
- use in well ventilated, but not windy areas
- reapply:

• after 80 minutes of swimming or sweating

• immediately after towel drying

• at least every 2 hours

- children under 6 months of age: ask a doctor
- Sun Protection Measures. Spending time in the sun increases your risk of skin cancer and early skin aging. To decrease this risk, regularly use a sunscreen with a broad-spectrum SPF of 15 or higher and other sun protection measures including:

• limit time in the sun, especially from 10 a.m. - 2 p.m.

• wearl long-sleeve shirts, pants, hats, and sunglasses

Other Information

- protect this product from excessive heat and direct sun
- may stain or damage some fabrics, materials or surfaces

Inactive Ingredients

SD alcohol 40-B, butyloctyl salicylate, acrylates/octylacrylamide copolymer, glycerin, saccharomyces/podophyllum peltatum ferment filtrate, caprylic/capric triglyceride, stearoxytrimethylsilane, tocopherol, panthenol, butylene glycol, fragrance

Questions or Comments?

Call toll free 1-800-527-7731

PACKAGE LABEL

H-E-B SOLUTIONS SUNSCREEN BANANA SPF 50 CONTINUOUS SPRAY

5.5 OZ (156g)

NDC 37808-912-37